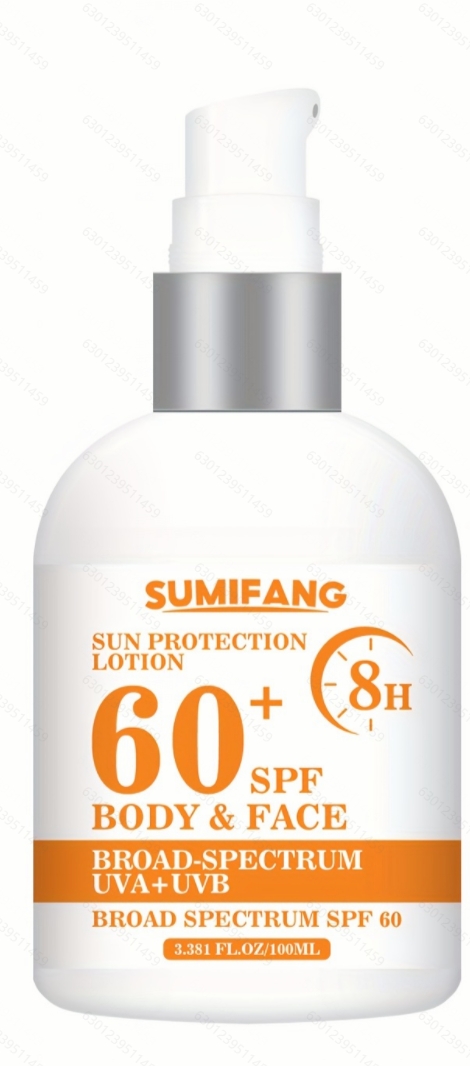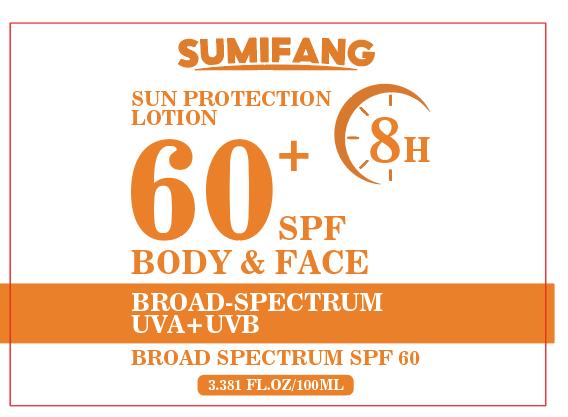 DRUG LABEL: LOTIONSUNPROTECTION
NDC: 84025-066 | Form: CREAM
Manufacturer: Guangzhou Yanxi Biotechnology Co., Ltd
Category: otc | Type: HUMAN OTC DRUG LABEL
Date: 20240712

ACTIVE INGREDIENTS: ZINC OXIDE 5 g/100 mL; BUTYLENE GLYCOL 3 g/100 mL
INACTIVE INGREDIENTS: WATER

DOSAGE AND ADMINISTRATION

use as a normal facial cream

WARNINGS

Keep out of Children

INACTIVE INGREDIENT

Aqua

INDICATIONS AND USAGE

For daily facial care

Keep out of Children

PURPOSE

May protect skin from the damaging effects of ultraviolet (UV) radiation